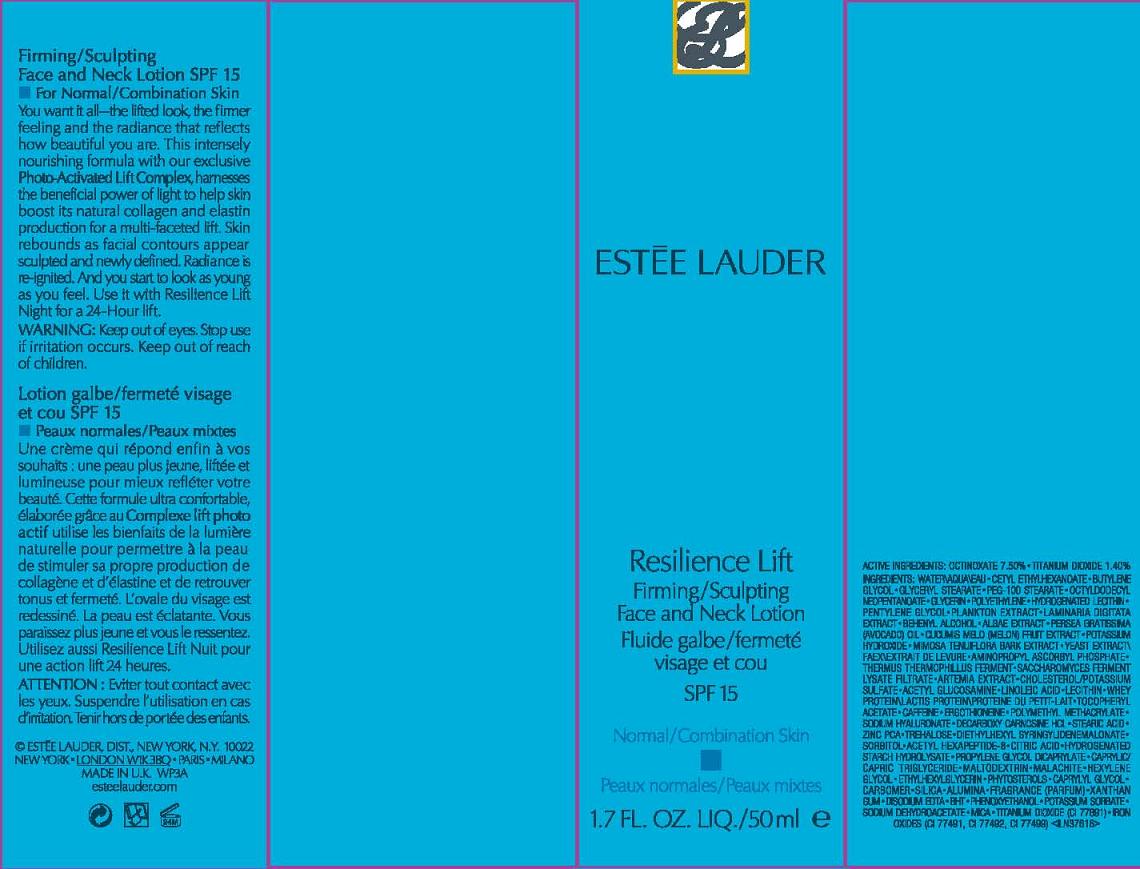 DRUG LABEL: RESILIENCE LIFT
NDC: 11559-013 | Form: LOTION
Manufacturer: ESTEE LAUDER INC
Category: otc | Type: HUMAN OTC DRUG LABEL
Date: 20110701

ACTIVE INGREDIENTS: OCTINOXATE 7.5 mL/100 mL; TITANIUM DIOXIDE 1.4 mL/100 mL
INACTIVE INGREDIENTS: WATER; CETYL ETHYLHEXANOATE; BUTYLENE GLYCOL; GLYCERYL MONOSTEARATE; PEG-100 STEARATE; OCTYLDODECYL NEOPENTANOATE; GLYCERIN; HYDROGENATED SOYBEAN LECITHIN; PENTYLENE GLYCOL; DOCOSANOL; SODIUM ALGINATE; AVOCADO OIL; MUSKMELON; POTASSIUM HYDROXIDE; MIMOSA TENUIFLORA BARK; YEAST; SACCHAROMYCES CEREVISIAE; CHOLESTEROL; POTASSIUM SULFATE; N-ACETYLGLUCOSAMINE; LINOLEIC ACID; LECITHIN, SOYBEAN; WHEY; ALPHA-TOCOPHEROL ACETATE; CAFFEINE; ERGOTHIONEINE; HYALURONATE SODIUM; STEARIC ACID; ZINC PIDOLATE; TREHALOSE; SORBITOL; ACETYL HEXAPEPTIDE-3; CITRIC ACID MONOHYDRATE; PROPYLENE GLYCOL DICAPRYLATE; MEDIUM-CHAIN TRIGLYCERIDES; MALTODEXTRIN; HEXYLENE GLYCOL; ETHYLHEXYLGLYCERIN; CAPRYLYL GLYCOL; CARBOMER HOMOPOLYMER TYPE C; SILICON DIOXIDE; ALUMINUM OXIDE; XANTHAN GUM; EDETATE DISODIUM; BUTYLATED HYDROXYTOLUENE; PHENOXYETHANOL; POTASSIUM SORBATE; SODIUM DEHYDROACETATE; MICA; FERRIC OXIDE RED

ACTIVE INGREDIENT

ACTIVE INGREDIENTS: OCTINOXATE 7.50% [] TITANIUM DIOXIDE 1.40%

INACTIVE INGREDIENT

INACTIVE NGREDIENTS: WATER [] CETYL ETHYLHEXANOATE [] BUTYLENE GLYCOL [] GLYCERYL STEARATE [] PEG-100 STEARATE [] OCTYLDODECYL NEOPENTANOATE [] GLYCERIN [] POLYETHYLENE [] HYDROGENATED LECITHIN [] PENTYLENE GLYCOL [] PLANKTON EXTRACT [] LAMINARIA DIGITATA EXTRACT [] BEHENYL ALCOHOL [] ALGAE EXTRACT [] PERSEA GRATISSIMA (AVOCADO) OIL [] CUCUMIS MELO (MELON) FRUIT EXTRACT [] POTASSIUM HYDROXIDE [] MIMOSA TENUIFLORA BARK EXTRACT [] YEAST EXTRACT\FAEX\EXTRAIT DE LEVURE [] AMINOPROPYL ASCORBYL PHOSPHATE [] THERMUS THERMOPHILLUS FERMENT [] SACCHAROMYCES FERMENT LYSATE FILTRATE [] ARTEMIA EXTRACT [] CHOLESTEROL/POTASSIUM SULFATE [] ACETYL GLUCOSAMINE [] LINOLEIC ACID [] LECITHIN [] WHEY PROTEIN\LACTIS PROTEIN\PROTEINE DU PETIT-LAIT [] TOCOPHERYL ACETATE [] CAFFEINE [] ERGOTHIONEINE [] POLYMETHYL METHACRYLATE [] SODIUM HYALURONATE [] DECARBOXY CARNOSINE HCL [] STEARIC ACID [] ZINC PCA [] TREHALOSE [] DIETHYLHEXYL SYRINGYLIDENEMALONATE [] SORBITOL [] ACETYL HEXAPEPTIDE-8 [] CITRIC ACID [] HYDROGENATED STARCH HYDROLYSATE [] PROPYLENE GLYCOL DICAPRYLATE [] CAPRYLIC/CAPRIC TRIGLYCERIDE [] MALTODEXTRIN [] MALACHITE [] HEXYLENE GLYCOL [] ETHYLHEXYLGLYCERIN [] PHYTOSTEROLS [] CAPRYLYL GLYCOL [] CARBOMER [] SILICA [] ALUMINA [] FRAGRANCE (PARFUM) [] XANTHAN GUM [] DISODIUM EDTA [] BHT [] PHENOXYETHANOL [] POTASSIUM SORBATE [] SODIUM DEHYDROACETATE [] MICA [] TITANIUM DIOXIDE (CI 77891) [] IRON OXIDES (CI 77491, CI 77492, CI 77499)

WARNINGS

WARNING: KEEP OUT OF EYES. STOP USE IF IRRITATION OCCURS. KEEP OUT OF REACH OF CHILDREN.

PACKAGE LABEL

PRINCIPAL DISPLAY PANEL:

ESTEE LAUDER

RESILIENCE LIFT

FIRMING/SCULPTING FACE AND NECK

LOTION

SPF15

NORMAL/COMBO SKIN

NET WT. 1.7 OZ LIQ/50 ML

ESTEE LAUDER, DISTR

NEW YORK, NY 10022